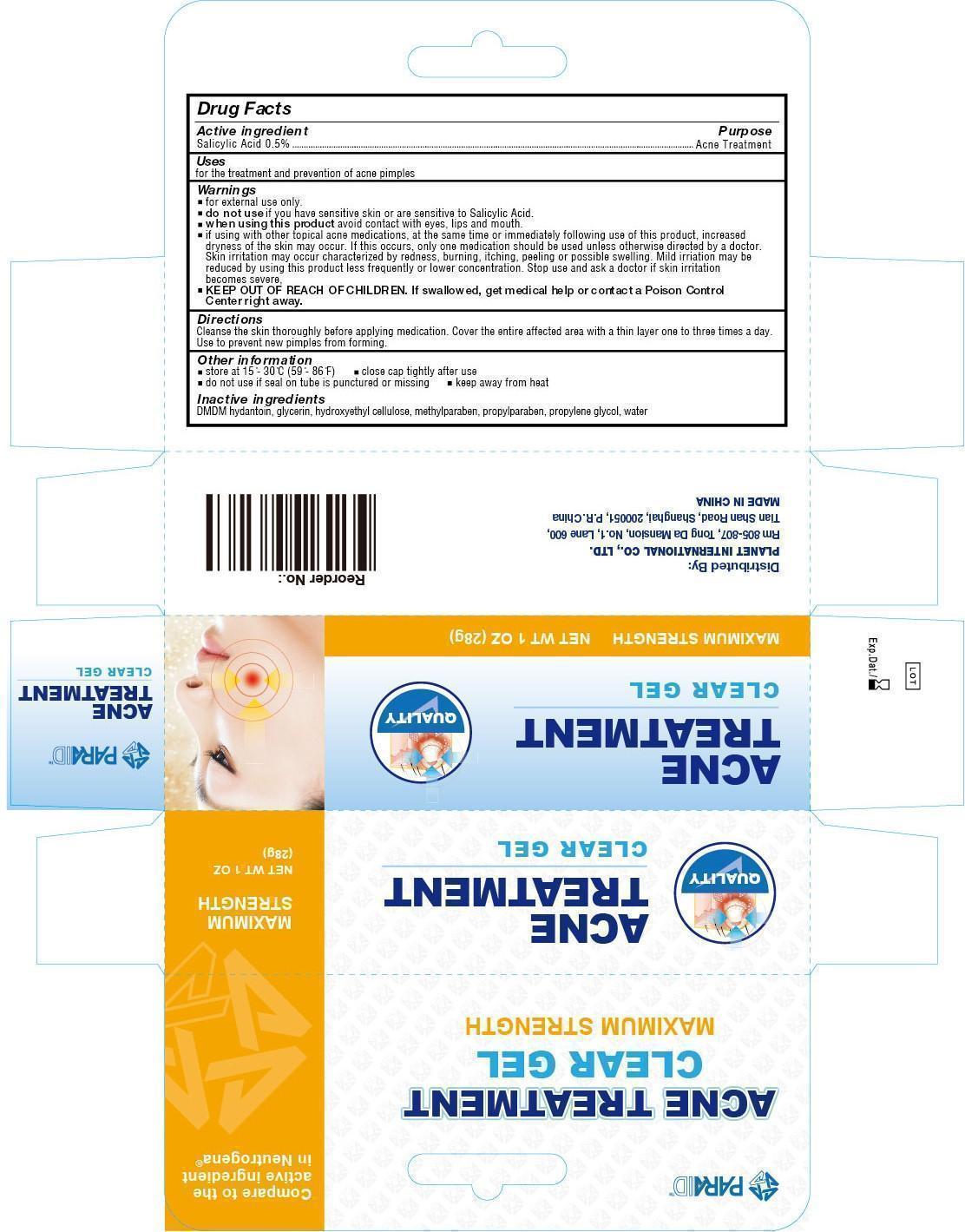 DRUG LABEL: Acne Treatment Clear Gel - Maximum Strength
NDC: 52486-010 | Form: GEL
Manufacturer: McCure Health Solutions Inc.
Category: otc | Type: HUMAN OTC DRUG LABEL
Date: 20161228

ACTIVE INGREDIENTS: SALICYLIC ACID 5 mg/1 g
INACTIVE INGREDIENTS: DMDM HYDANTOIN; GLYCERIN; METHYLPARABEN; PROPYLPARABEN; PROPYLENE GLYCOL; WATER

Acne Treatment Clear Gel - Maximum Strength

Active ingredient

Salicylic Acid 0.5%

Purpose

Acne Treatment

Uses

for the treatment and prevention of acne pimples

Warnings

for external use only.

do not use

if you have sensitive skin or are sensitive to Salicylic Acid.

When using this product

avoid contact with eyes, lips and mouth.

- if using with other topical acne medications, at the same time or immediately following use of this product, increased dryness of the skin may occur. If this occurs, only one medication should be used unless otherwise directed by a doctor. Skin irritation may occur characterized by redness, burning, itching, peeling or possible swelling. Mild irriation may be reduced by using this product less frequently or lower concentration. Stop use and ask a doctor if skin irritation becomes severe.

KEEP OUT OF REACH OF CHILDREN.

If swallowed, ger medical help or contact a Poison Control Center right away.

Directions

Cleanse the skin thoroughly before applying medication. Cover the entire affected area with a thin layer one to three times day. Use to prevent new pimples from forming.

Other information

- store at 15 - 30 C (59 - 86 F)
- close cap tightly after use
- do not use if seal on tube is punctured or missing
- keep away from heat

Inactive ingredients

DMDM HYDANTOIN, GLYCERIN, HYDROXYETHYL CELLULOSE, METHYLPARABEN, PROPYLPARABEN, PROPYLENE GLYCOL, WATER